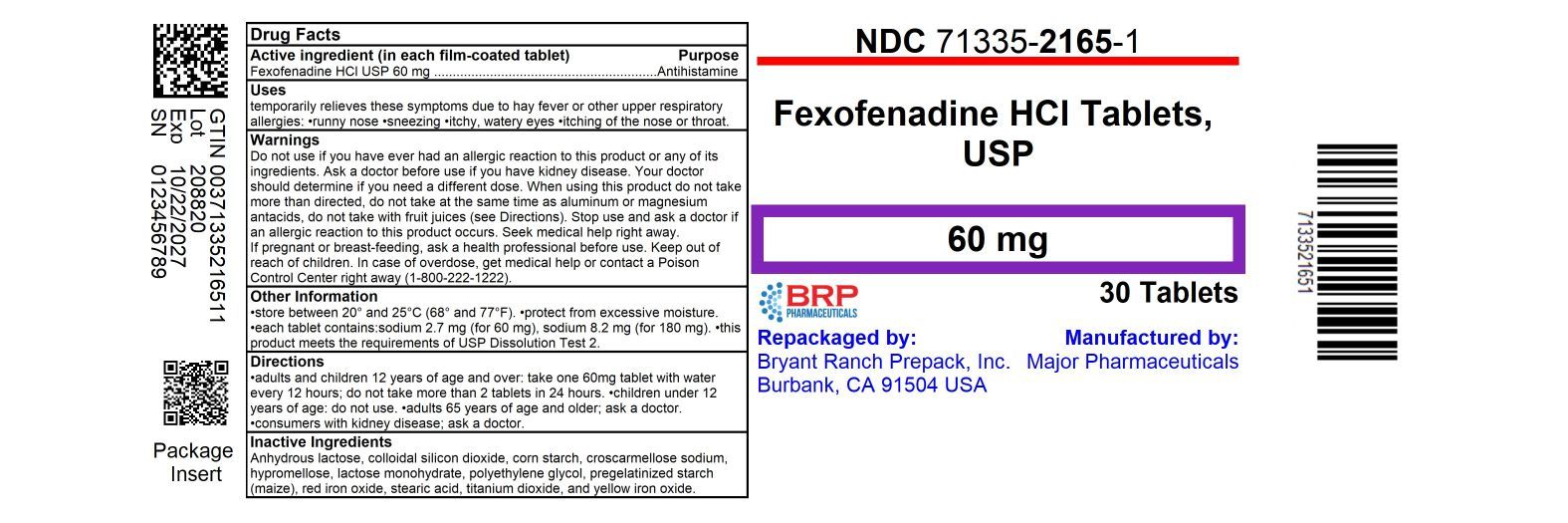 DRUG LABEL: fexofenadine hcl
NDC: 71335-2165 | Form: TABLET, FILM COATED
Manufacturer: Bryant Ranch Prepack
Category: otc | Type: HUMAN OTC DRUG LABEL
Date: 20251022

ACTIVE INGREDIENTS: FEXOFENADINE HYDROCHLORIDE 60 mg/1 1
INACTIVE INGREDIENTS: ANHYDROUS LACTOSE; SILICON DIOXIDE; STARCH, CORN; CROSCARMELLOSE SODIUM; LACTOSE MONOHYDRATE; STEARIC ACID; HYPROMELLOSE, UNSPECIFIED; POLYETHYLENE GLYCOL, UNSPECIFIED; FERRIC OXIDE RED; TITANIUM DIOXIDE; FERRIC OXIDE YELLOW

® Tablets

ALLERGY Active ingredient (in each film-coated tablet)

Fexofenadine HCl USP 60 mg
Fexofenadine HCl USP 180 mg

Purpose

Antihistamine

Uses

temporarily relieves these symptoms due to hay fever or other upper respiratory allergies:

- runny nose
- sneezing
- itchy, watery eyes
- itching of the nose or throat

Warnings

Do not use

if you have ever had an allergic reaction to this product or any of its ingredients.

Ask a doctor before use if you have

kidney disease. Your doctor should determine if you need a different dose.

When using this product

- do not take more than directed
- do not take at the same time as aluminum or magnesium antacids
- do not take with fruit juices (see Directions)

Stop use and ask a doctor if

an allergic reaction to this product occurs. Seek medical help right away.

If pregnant or breast-feeding,

ask a health professional before use.

Keep out of reach of children.

In case of overdose, get medical help or contact a Poison Control Center right away (1-800-222-1222).

Directions

Directions (for 60mg)

adults and children 12 years of age and over | take one 60mg tablet with water every 12 hours; do not take more than 2 tablets in 24 hours
children under 12 years of age | do not use
adults 65 years of age and older | ask a doctor
consumers with kidney disease | ask a doctor

Directions (for 180mg)

adults and children 12 years of age and over | take one 180mg tablet with water once a day; do not take more than 1 tablet in 24 hours
children under 12 years of age | do not use
adults 65 years of age and older | ask a doctor
consumers with kidney disease | ask a doctor

Other information

- store between 20° and 25°C (68° and 77°F)
- protect from excessive moisture
- each tablet contains:sodium 2.7 mg (for 60 mg), sodium 8.2 mg (for 180 mg)
- this product meets the requirements of USP Dissolution Test 2

Inactive ingredients

anhydrous lactose, colloidal silicon dioxide, corn starch, croscarmellose sodium, hypromellose, lactose monohydrate, polyethylene glycol, pregelatinized starch (maize), red iron oxide, stearic acid, titanium dioxide, and yellow iron oxide

Questions or comments?

Call toll-free 1-888-588-1418
Monday-Friday 9AM-7PM EST

Distributed by: MAJOR®PHARMACEUTICALS
Indianapolis, IN 46268
(800) 616-2471
www.majorpharmaceuticals.com

HOW SUPPLIED

Fexofenadine Hydrochloride 60mg Tablets

- NDC 71335-2165-1: 30 Tablets in a BOTTLE
- NDC 71335-2165-2: 10 Tablets in a BOTTLE
- NDC 71335-2165-3: 60 Tablets in a BOTTLE
- NDC 71335-2165-4: 90 Tablets in a BOTTLE
- NDC 71335-2165-5: 14 Tablets in a BOTTLE
- NDC 71335-2165-6: 20 Tablets in a BOTTLE
- NDC 71335-2165-7: 12 Tablets in a BOTTLE

store between 20° and 25°C (68° and 77°F). protect from excessive moisture.

Repackaged/Relabeled by:
Bryant Ranch Prepack, Inc.
Burbank, CA 91504

PACKAGE LABEL

Fexofenadine Hydrochloride 60mg Tablets